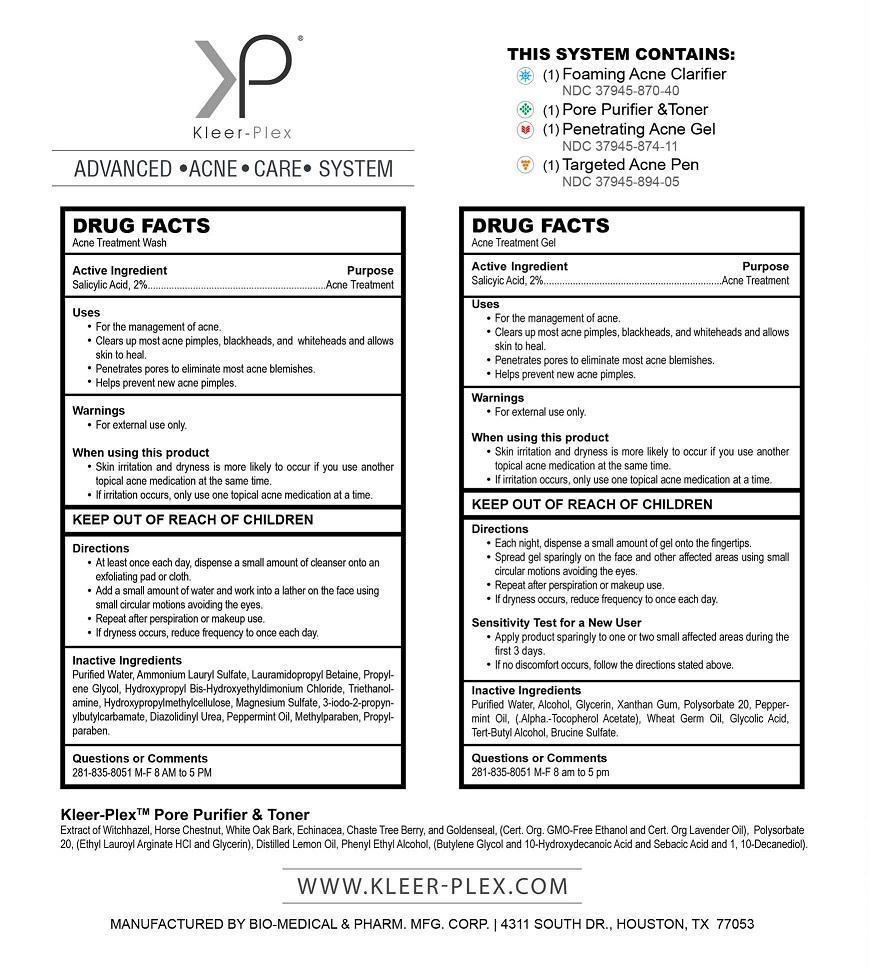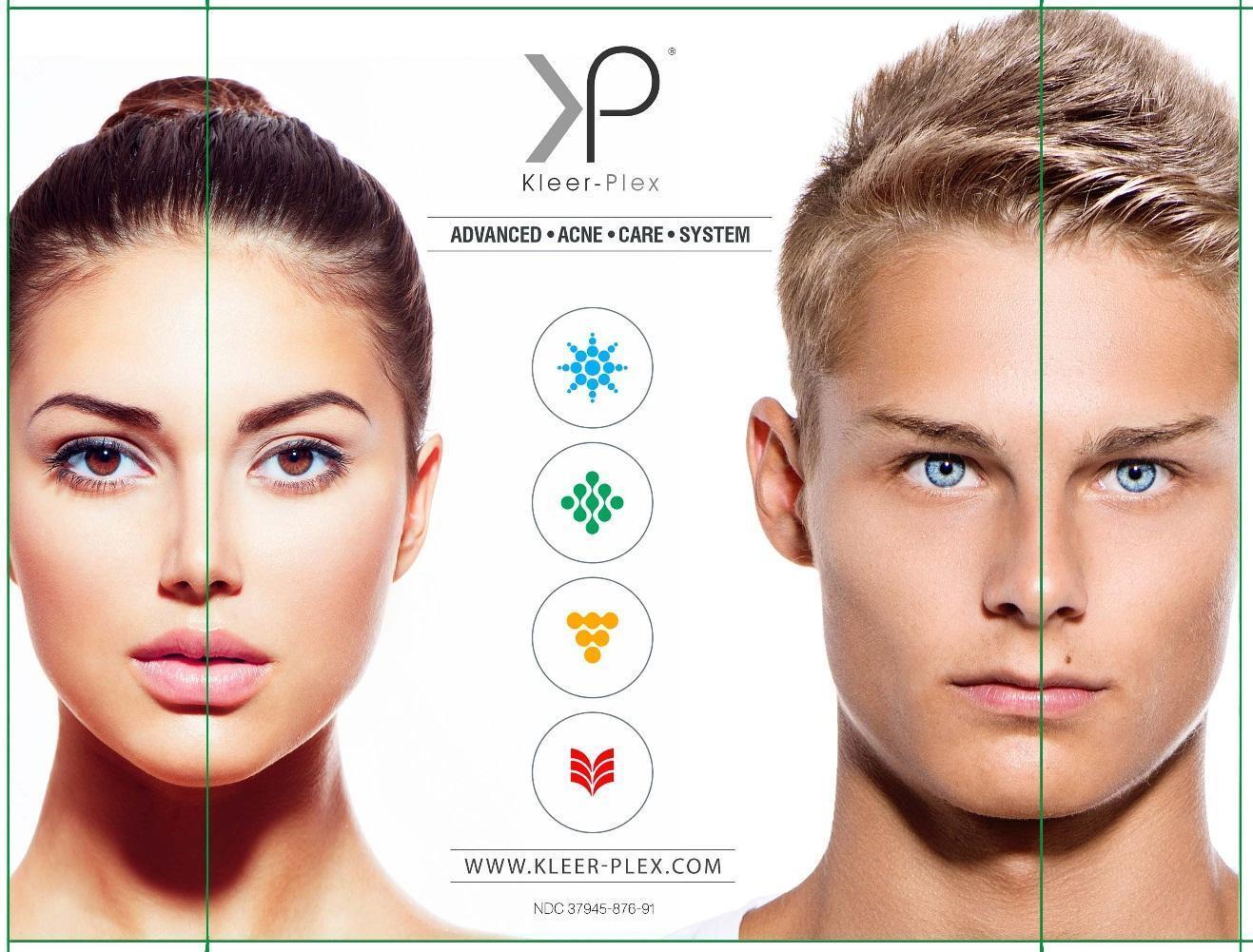 DRUG LABEL: Kleer-Plex Advanced Acne Care System
NDC: 37945-876 | Form: KIT | Route: TOPICAL
Manufacturer: Bio-Medical & Pharmaceutical Manufacturing Corporation
Category: otc | Type: HUMAN OTC DRUG LABEL
Date: 20141103

ACTIVE INGREDIENTS: SALICYLIC ACID 20 mg/1 mL; SALICYLIC ACID 20 mg/1 mL; SALICYLIC ACID 20 mg/1 mL
INACTIVE INGREDIENTS: WATER; AMMONIUM LAURYL SULFATE; LAURAMIDOPROPYL BETAINE; PROPYLENE GLYCOL; HYDROXYPROPYL BIS-HYDROXYETHYLDIMONIUM CHLORIDE; TROLAMINE; HYPROMELLOSES; MAGNESIUM SULFATE; IODOPROPYNYL BUTYLCARBAMATE; DIAZOLIDINYL UREA; PEPPERMINT OIL; METHYLPARABEN; PROPYLPARABEN; WATER; ALCOHOL; GLYCERIN; XANTHAN GUM; POLYSORBATE 20; PEPPERMINT OIL; .ALPHA.-TOCOPHEROL ACETATE; WHEAT GERM OIL; GLYCOLIC ACID; TERT-BUTYL ALCOHOL; BRUCINE SULFATE; WATER; ALCOHOL; GLYCERIN; XANTHAN GUM; POLYSORBATE 20; PEPPERMINT OIL; .ALPHA.-TOCOPHEROL ACETATE; WHEAT GERM OIL; GLYCOLIC ACID; TERT-BUTYL ALCOHOL; BRUCINE SULFATE

Kleer-Plex Advanced Acne Care System

THIS SYSTEM CONTAINS:

(1) Foaming Acne Clarifier

NDC 37945-870-40

(1) Pore Purifier & Toner

(1) Penetrating Acne Gel

NDC 37945-874-11

(1) Targeted Acne Pen

NDC 37945-894-05

DRUG FACTS

Acne Treatment Wash and Acne Treatment Gel

Active Ingredient

Salicylic Acid, 2%

Purpose

Acne Treatment

Uses

- For the management of acne.
- Clears up most acne pimples, blackheads, and whiteheads and allows skin to heal.
- Penetrates pores to eliminate most acne blemishes.
- Helps prevent new acne pimples.

Warnings

For external use only.

When using this product

- Skin irritation and dryness is more likely to occur if you use another topical acne medication at the same time.
- If irritation occurs, only use one topical acne medication at a time.

KEEP OUT OF REACH OF CHILDREN

Directions

Acne Treatment Wash

- At least once each day, dispense a small amount of cleanser onto an exfoliating pad or cloth.
- Add a small amount of water and work into a lather on the face using small circular motions avoiding the eyes.
- Repeat after perspiration or makeup use.
- If dryness occurs, reduce frequency to once each day.

Acne Treatment Gel

- Each night, dispense a small amount of gel onto the fingertips.
- Spread gel sparingly on the face and other affected areas using small circular motions avoiding the eyes.
- Repeat after perspiration or makeup use.
- If dryness occurs, reduce frequency to once each day.

Sensitivity Test for a New User - Acne Treatment Gel

- Apply product sparingly to one or two small affected areas during the first 3 days.
- If no discomfort occurs, follow the directions stated above.

Inactive Ingredients

Acne Treatment Wash

Purified Water, Ammonium Lauryl Sulfate, Lauramidopropyl Betaine, Propylene Glycol, Hydroxypropyl Bis-Hydroxyethyldimonium Chloride, Triethanolamine, Hydroxypropylmethylcellulose, Magnesium Sulfate, 3-iodo-2-propynylbutylcarbamate, Diazolidinyl Urea, Peppermint Oil, Methylparaben, Propylparaben.

Acne Treatment Gel

Purified Water, Alcohol, Glycerin, Xanthan Gum, Polysorbate 20, Peppermint Oil, (.Alpha.-Tocopherol Acetate), Wheat Germ Oil, Glycolic Acid, Tert-Butyl Alcohol, Brucine Sulfate.

Questions or Comments

281-835-8051

M-F 8 AM to 5 PM

Kleer-Plex Advanced Acne System Principal Display Panel NDC# 37945-876-91

KleerPlexFront.jpg KleerPlexBack.jpg